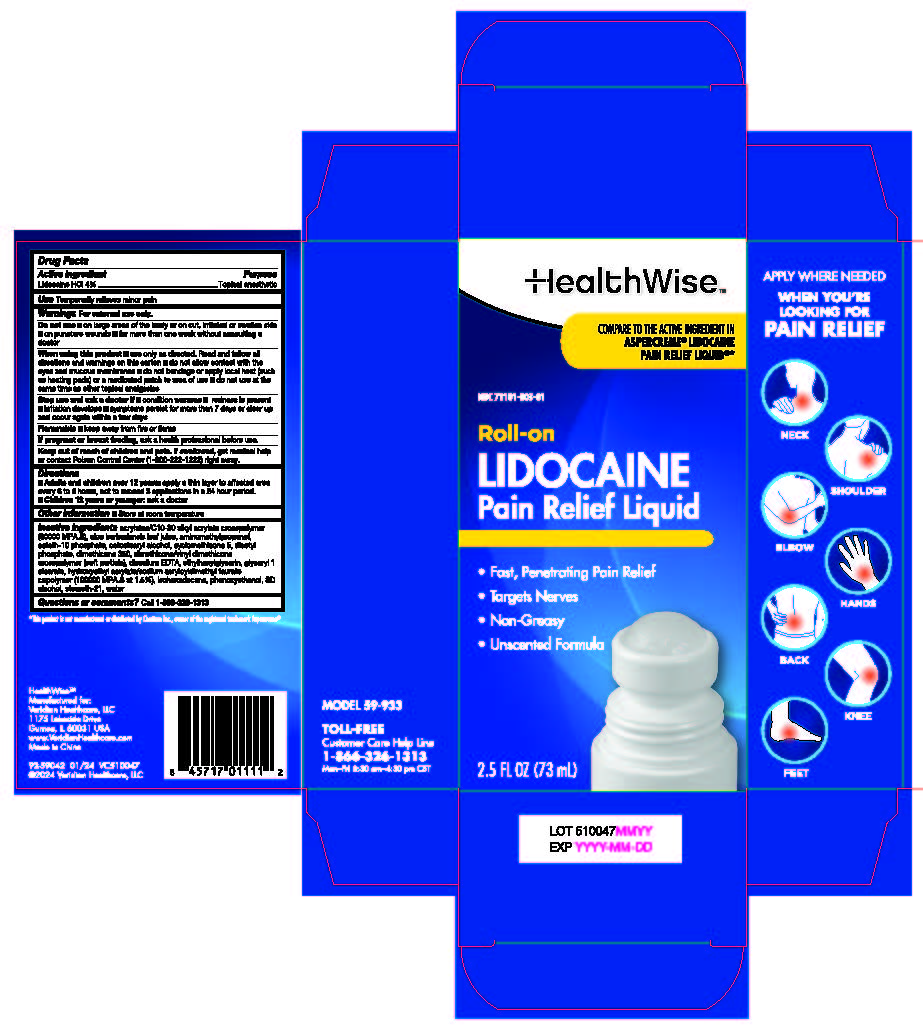 DRUG LABEL: HealthWise Roll-On Lidocaine Pain Relief Liquid
NDC: 71101-003 | Form: LIQUID
Manufacturer: Veridian Healthcare
Category: otc | Type: HUMAN OTC DRUG LABEL
Date: 20250918

ACTIVE INGREDIENTS: LIDOCAINE 4 g/1 mL
INACTIVE INGREDIENTS: GLYCERYL 1-STEARATE; ALOE VERA LEAF; AMINOMETHYLPROPANOL; ISOHEXADECANE; HYDROXYETHYL ACRYLATE/SODIUM ACRYLOYLDIMETHYL TAURATE COPOLYMER (45000 MPA.S AT 1%); ALCOHOL; CYCLOMETHICONE 5; WATER; ACRYLATES/C10-30 ALKYL ACRYLATE CROSSPOLYMER (60000 MPA.S); DIHEXADECYL PHOSPHATE; DIMETHICONE 350; ETHYLHEXYLGLYCERIN; DIMETHICONE/VINYL DIMETHICONE CROSSPOLYMER (SOFT PARTICLE); CETETH-10 PHOSPHATE; EDETATE DISODIUM ANHYDROUS; CETOSTEARYL ALCOHOL; PHENOXYETHANOL; LAVENDER OIL; STEARETH-21

HealthWise Roll-On Lidocaine Pain Relief Liquid

HealthWise 4% Lidocaine Pain Relief Roll-on

Active ingredient

Lidocaine 4%

Purpose

Topical analgesic

Uses

temporarily relieves minor pain

Warnings

For external use only

When using this product

- use only as directed. Read and follow all directions and warnings on this carton.
- do not allow contact with the eyes and mucus membranes
- do not bandage tightly or apply local heat (such as heating pads) or a medicated patch to the area of use
- do not use at the same time as other topical analgesics

Stop use and ask a doctor if

- condition worsens
- redness is present
- irritation develops
- symptoms persist for more than 7 days or clear up and occur again within a few days

Flammable■ Keep away from fire or flame

If pregnant or breast-feeding,

ask a health professional before use.

Keep out of reach of children.

If swallowed, get medical help or contact a Poison Control Center (1-800-222-1222) right away.

Directions

adults and children over 12 years:

- apply a thin layer to affected area every 6 to 8 hours, not to exceed 3 applications in a 24-hour period

children 12 years or younger:ask a doctor

Inactive ingredients

Inactive ingredients acrylates/C10-30 alkyl acrylate crosspolymer (60000 MPA.S), aloe barbadensis leaf juice, aminomethylpropanol, ceteth-10 phosphate, cetostearyl alcohol, cyclomethicone 5, dicetyl phosphate, dimethicone 350, dimethicone/vinyl dimethicone crosspolymer (soft particle), disodium EDTA, ethylhexylglycerin, glyceryl 1 stearate, hydroxyethyl acrylate/sodium acryloyldimethyl taurate copolymer (100000 MPA.S at 1.5%), isohexadecane, phenoxyethanol, SD alcohol, steareth-21, water

Questions or comments

Call 1-866-326-1313